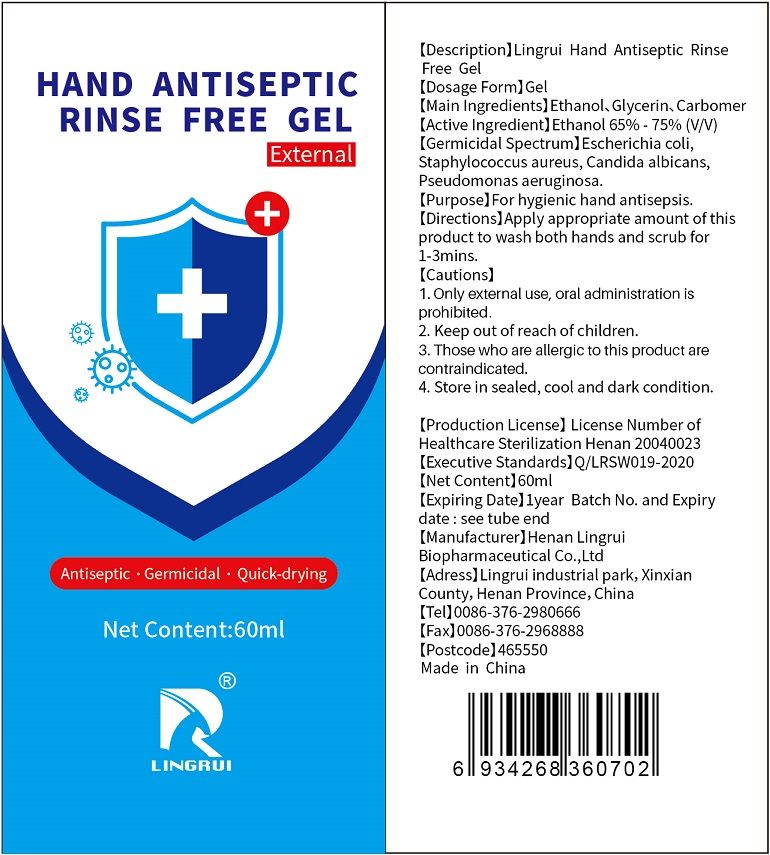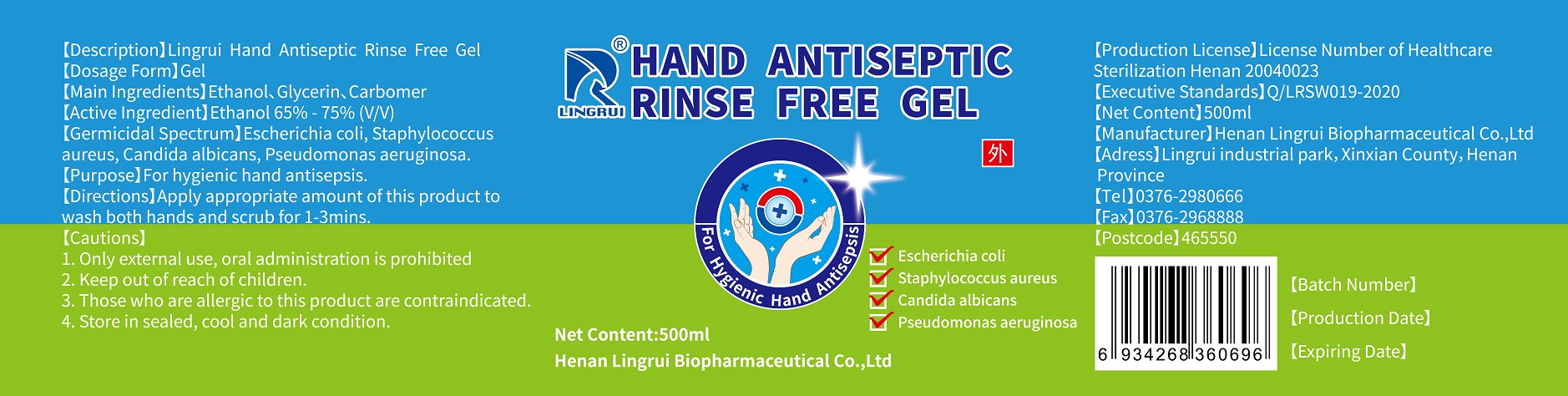 DRUG LABEL: Lingrui Hand Antiseptic Rinse Free
NDC: 42217-0110 | Form: GEL
Manufacturer: Henan Lingrui Biopharmaceutical Co., Ltd
Category: otc | Type: HUMAN OTC DRUG LABEL
Date: 20200427

ACTIVE INGREDIENTS: ALCOHOL 40.6 mL/60 mL
INACTIVE INGREDIENTS: GLYCERIN; TRICLOSAN; TROLAMINE; WATER; CARBOMER INTERPOLYMER TYPE A (ALLYL SUCROSE CROSSLINKED)

LingRui, Sanitizer, Ethanol 68%, Gel

Active Ingredient(s)

Ethanol 68% v/v. Purpose: Antiseptic

Purpose

For hygienic hand antisepsis.

Use

Hand Sanitizer to help reduce bacteria that potentially can cause disease. For use when soap and water are not available.

Warnings

Flammable. For external use only. Keep away from heat or flame.

1. Only external use, oral administration is prohibited.

2. Keep out of reach of children.

3. Those who are allergic to this product (alcohol, ethanol) are contraindicated.

Do not use

- on children less than 2 months of age
- on open skin wounds
- in the eyes. in case of contact, rinse eyes thoroughly with water

When using this product keep out of eyes, ears, and mouth.

In case of contact with eyes, rinse eyes thoroughly with water.

Stop use and ask a doctor if irritation and redness develop and persist for more than 72 hours.

Keep out of reach of children. If swallowed, get medical help or contact a Poison Control Center right away.

Directions

Apply appropriate amount of this product to wash both hands and scrub for 1-3mins.

Other information

Store in sealed, cool and dark condition.

Inactive ingredients

Purified Water, Glycerol, Carbomer, Trolamine, Triclosan.